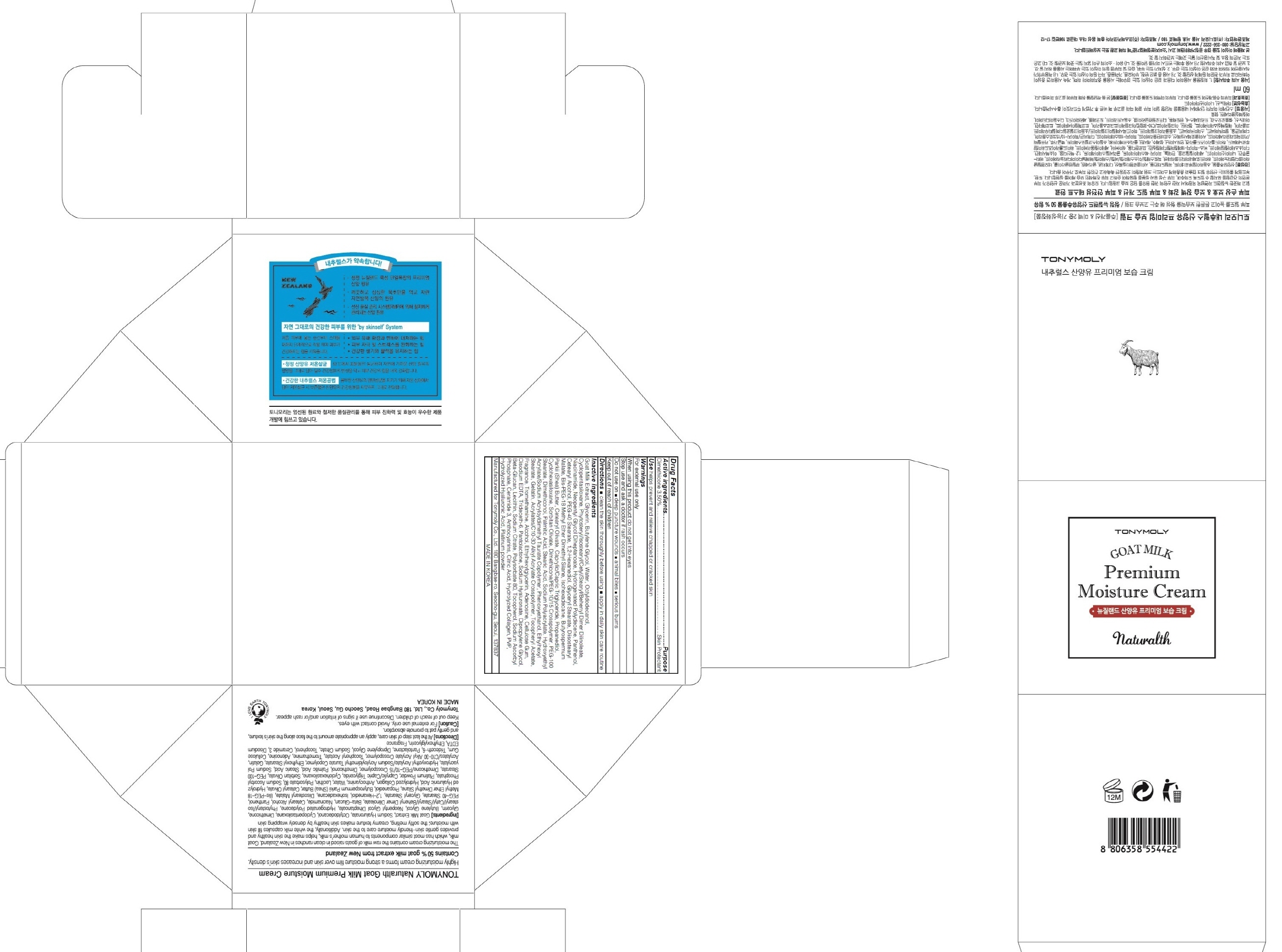 DRUG LABEL: TONYMOLY NATURALTH GOAT MILK PREMIUM MOISTURE
NDC: 59078-230 | Form: CREAM
Manufacturer: TONYMOLY CO.,LTD
Category: otc | Type: HUMAN OTC DRUG LABEL
Date: 20160120

ACTIVE INGREDIENTS: Dimethicone 2.10 g/60 mL
INACTIVE INGREDIENTS: Goat Milk; Glycerin

ACTIVE INGREDIENT

Active ingredients: Dimethicone 3.50%

INACTIVE INGREDIENT

Inactive ingredients: Goat Milk Extract, Glycerin, Butylene Glycol, Water, Octyldodecanol, Cyclopentasiloxane, Phytosteryl/Isostearyl/Cetyl/Stearyl/Behenyl Dimer Dilinoleate, Niacinamide, Neopentyl Glycol Diheptanoate, Hydrogenated Polydecene, Panthenol, Cetearyl Alcohol, PEG-40 Stearate, 1,2-Hexanediol, Glyceryl Stearate, Diisostearyl Malate, Bis-PEG-18 Methyl Ether Dimethyl Silane, Isohexadecane, Butyrospermum Parkii (Shea) Butter, Cetearyl Olivate, Caprylic/Capric Triglyceride, Propanediol, Cyclohexasiloxane, Sorbitan Olivate, Dimethicone/PEG-10/15 Crosspolymer, PEG-100 Stearate, Dimethiconol, Palmitic Acid, Stearic Acid, Sodium Polyacrylate, Hydroxyethyl Acrylate/Sodium Acryloyldimethyl Taurate Copolymer, Phenoxyethanol, Ethylhexyl Stearate, Gelatin, Acrylates/C10-30 Alkyl Acrylate Crosspolymer, Tocopheryl Acetate, Fragrance, Tromethamine, Alcohol, Ethylhexylglycerin, Adenosine, Cellulose Gum, Disodium EDTA, Trideceth-6, Pantolactone, Sodium Hyaluronate, Dipropylene Glycol, Beta-Glucan, Lecithin, Sodium Citrate, Polysorbate 80, Tocopherol, Sodium Ascorbyl Phosphate, Ceramide 3, Anthocyanins, Citric Acid, Hydrolyzed Collagen, PVP, Hydrolyzed Hyaluronic Acid, Platinum powder

PURPOSE

Purpose: Skin Protectant

WARNINGS

Warnings: For external use only

When using this product do not get into eyes

Stop use and ask a doctor if rash occurs

Do not use on - deep puncture wounds - animal bites - serious burns

Keep out of reach of children

KEEP OUT OF REACH OF CHILDREN

Use

Use: helps prevent and relieve chapped or cracked skin

Directions

Directions: - clean the skin thoroughly before using - apply in daily skin care routined